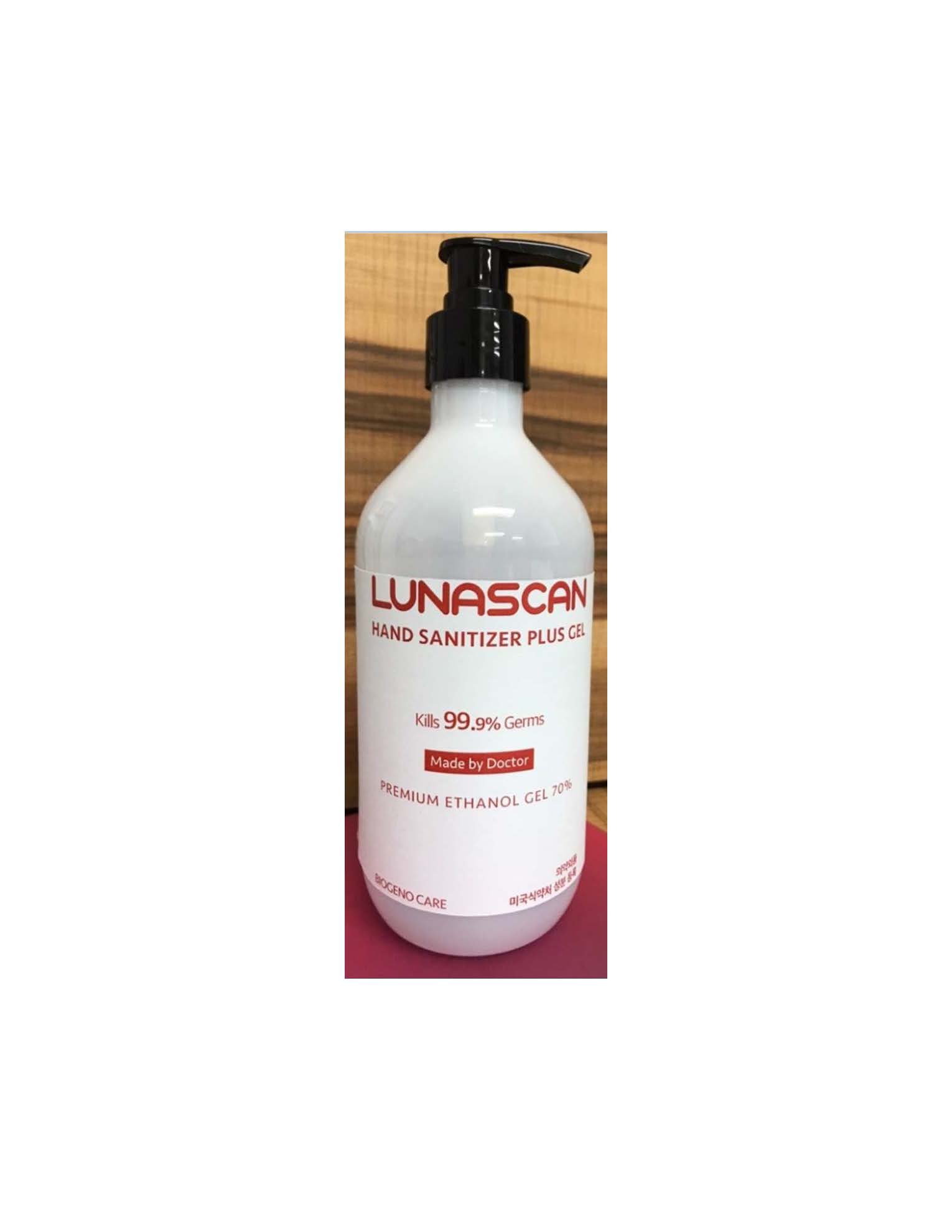 DRUG LABEL: Biogeno Care Hand Sanitizer Gel (Ethanol)
NDC: 77637-400 | Form: GEL
Manufacturer: DERMACOS KOREA
Category: otc | Type: HUMAN OTC DRUG LABEL
Date: 20210330

ACTIVE INGREDIENTS: ALCOHOL 70 mL/100 mL
INACTIVE INGREDIENTS: ALOE VERA LEAF; GREEN TEA LEAF; GLYCERIN; WATER; TROLAMINE; HYALURONATE SODIUM; CARBOMER HOMOPOLYMER, UNSPECIFIED TYPE

Active Ingredient(s)

Alcohol 70% v/v. Purpose: Antimicrobial

Purpose

Antimicrobial, Hand Sanitizer

Use

Hand sanitizer to help reduce bacteria on the skin.
Recommended for repeated use.

Warnings

For external use only. Flammable. Keep away from heat or flame

Do not use

- in children less than 2 months of age
- on open skin wounds

When using this product keep out of eyes, ears, and mouth. In case of contact with eyes, rinse eyes thoroughly with water.
Stop use and ask a doctor if irritation or rash occurs. These may be signs of a serious condition.
Keep out of reach of children. If swallowed, get medical help or contact a Poison Control Center right away.

Stop use and ask a doctor if irritation or rash occurs. These may be signs of a serious condition.

Keep out of reach of children. If swallowed, get medical help or contact a Poison Control Center right away.

Directions

- Put enough product in your palm to cover hands and rub hands together briskly until dry.
- Children under 6 years of age should be supervised when using this product.
- Not recommended for infants.

Other information

- Store at room temperature (33.8oF-86oF, 1oC-30oC) and avoid cold or dry place.
- May discolor certain fabrics or surfaces.
- Harmful to wood finishes and plastics.

Inactive ingredients

Aloe Vera Gel, Carbomer, Fragrance (Lemon), Glycerin, Green Tea Extract, Purified Water, Rosa Damascena (Rose) Flower Water, Sodium Hyaluronate, Triethanolamine.